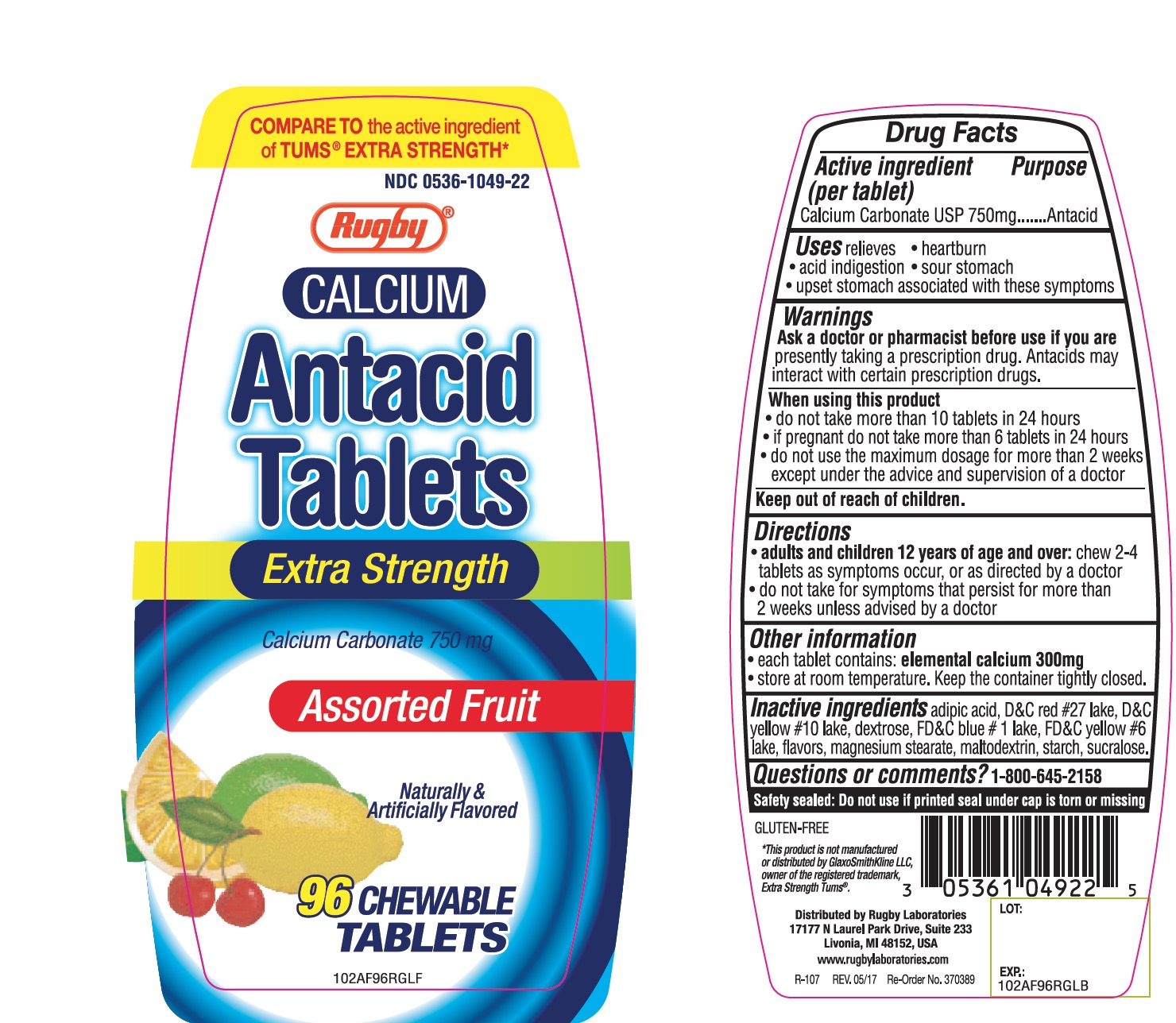 DRUG LABEL: calcium antacidextra strength

NDC: 0536-1049 | Form: TABLET, CHEWABLE
Manufacturer: Rugby Laboratories
Category: otc | Type: HUMAN OTC DRUG LABEL
Date: 20251203

ACTIVE INGREDIENTS: CALCIUM CARBONATE 750 mg/1 1
INACTIVE INGREDIENTS: ADIPIC ACID; D&C RED NO. 27; D&C YELLOW NO. 10; DEXTROSE, UNSPECIFIED FORM; FD&C BLUE NO. 1; FD&C YELLOW NO. 6; MAGNESIUM STEARATE; MALTODEXTRIN; STARCH, CORN; SUCRALOSE

Rugby. Calcium Antacid Tablets Drug Facts

Active ingredient (per tablet)

Calcium Carbonate USP 750mg

Purpose

Antacid

Uses

relieves

- heartburn
- sour stomach
- acid indigestion
- upset stomach associated with these symptoms

Warnings

Ask a doctor or pharmacist before use if you are

- presently taking a prescription drug. Antacids may interact with certain prescription drugs.

When using this product

- do not take more than 10 tablets in 24 hours
- if pregnant do not take more than 6 tablets in 24 hours
- do not use the maximum dosage for more than 2 weeks except under the advice and supervision of a doctor

Directions

- adults and children 12 years of age and over: chew 2 - 4 tablets as symptoms occur, or as directed by a doctor
- do not take for symptoms that persist for more than 2 weeks unless advised by a doctor

Other information

- each tablet contains: elemental calcium 300 mg
- Store at room temperature. Keep the container tightly closed.

Inactive ingredients

adipic acid, D&C red #27lake, D&C yellow#10 lake, dextrose, FD&C blue #1 lake, FD&C yellow#6 lake, flavors, magnesium stearate, maltodextrin, starch, sucralose

Questions or comments?

1-800-645-2158

Principal Display Panel

SAFETY SEALED. DO NOT USE IF PRINTED SEAL UNDER CAP IS TORN OR MISSING.

COMPARE TO the active ingredient of TUMS® EXTRA STRENGTH

NDC 0536-1049-22

Rugby®

CALCIUM

Antacid

Tablets

Extra Strength

Calcium Carbonate 750 mg

ASSORTED FRUIT

Naturally &Artificially Flavored

96 Chewable TABLETS

GLUTEN-FREE

*This product is not manufactured or distributed by GlaxoSmithKline LLC,

Owner of the registered trademark,

Extra Strength Tums®

Distributed by Rugby laboratories

17177 n Laurel Park Drive, Suite 233

Livonia, MI, 48152, USA

www.rugbylaboratories.com